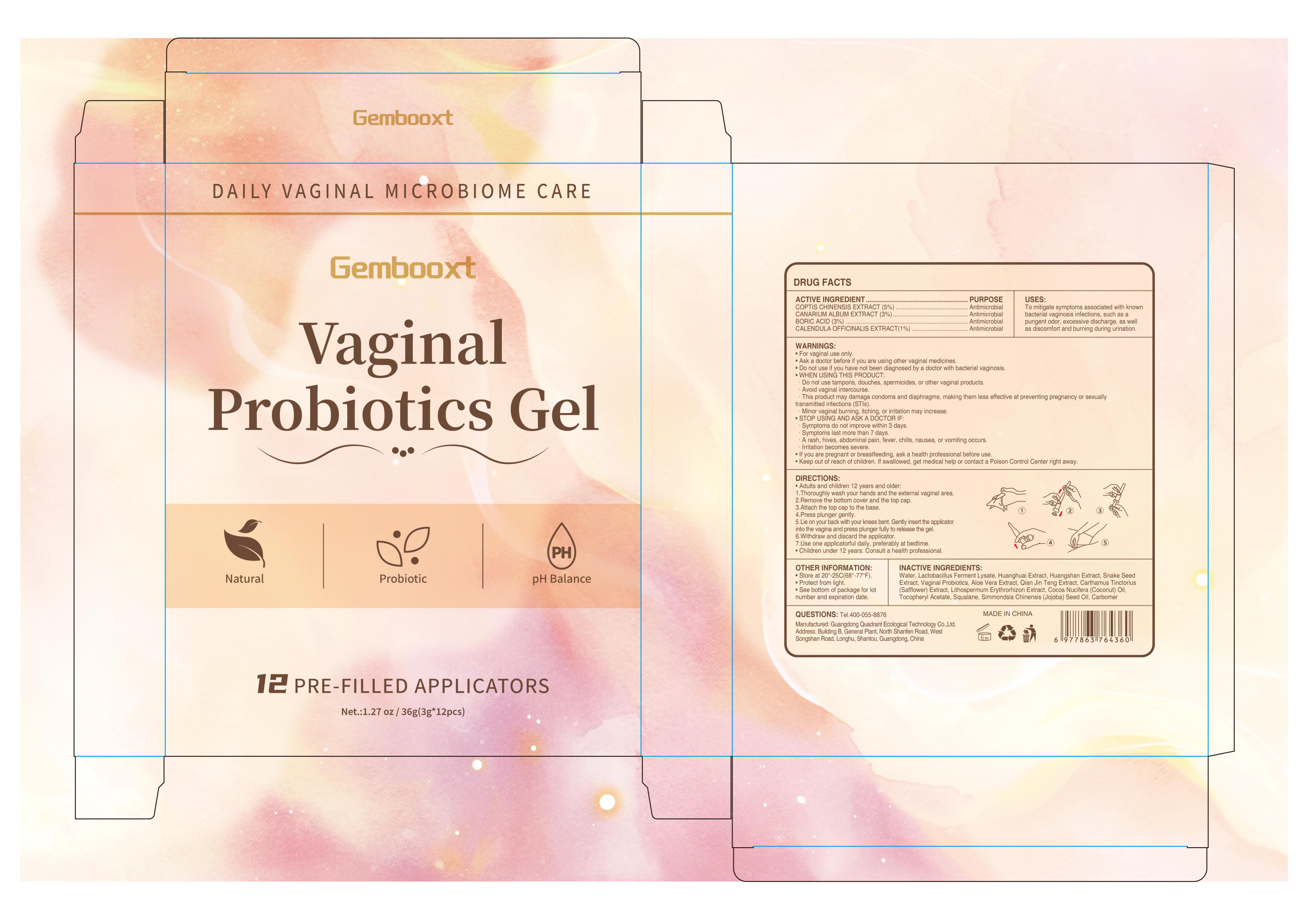 DRUG LABEL: Gembooxt Vaginal Probiotics Gel
NDC: 76986-021 | Form: GEL
Manufacturer: Guangdong Quadrant Ecological Technology Co., Ltd.
Category: otc | Type: HUMAN OTC DRUG LABEL
Date: 20251219

ACTIVE INGREDIENTS: BORIC ACID 0.03 g/1 g; COPTIS CHINENSIS ROOT 0.05 g/1 g; CANARIUM ALBUM WHOLE 0.03 g/1 g; CALENDULA OFFICINALIS FLOWER 0.01 g/1 g
INACTIVE INGREDIENTS: SQUALANE; CARBOMER; CARTHAMUS TINCTORIUS FLOWER BUD; LIMOSILACTOBACILLUS FERMENTUM; WATER; ALOE VERA LEAF; STEPHANIA JAPONICA WHOLE; COCONUT OIL; .ALPHA.-TOCOPHEROL ACETATE; SENNA ALEXANDRINA SEED; LITHOSPERMUM ERYTHRORHIZON ROOT; SIMMONDSIA CHINENSIS (JOJOBA) SEED OIL

76986-021 Gembooxt Vaginal Probiotics Gel

ACTIVE INGREDIENT

COPTIS CHINENSIS EXTRACT 5%
CANARIUM ALBUM EXTRACT 3%
BORIC ACID 3
CALENDULA OFFICINALIS EXTRACT 1%

PURPOSE

Antimicrobial

INDICATIONS AND USAGE

To mitigate symptoms associated with known bacterial vaginosis infections, such as a pungent odor, excessive discharge, as well as discomfort and burning during urination.

WARNINGS

For vaginal use only.

Do not use if you have not been diagnosed by a doctor with bacterial vaginosis.

Ask a doctor before if you are using other vaginal medicines.
WHEN USING THIS PRODUCT:
Do not use tampons, douches, spermicides, or other vaginal products.
Avoid vaginal intercourse.
This product may damage condoms and diaphragms, making them less efective at preventing pregnancy or sexually transmitted infections (STls)
Minor vaginal burning, itching, or irritation may increase.

If you are pregnant or breastfeeding, ask a health professional before use.

STOP USING AND ASK A DOCTOR IF:
Symptoms do not improve within 3 days.
Symptoms last more than 7 days
A rash, hives, abdominal pain, fever, chills, nausea, or vomiting occurs
lrritation becomes severe.

Keep out of reach of children. lf swallowed, get medical help or contact a Poison Control Center riaht away.

DOSAGE AND ADMINISTRATION

Adults and children 12 years and older:
1.Thoroughly wash your hands and the external vaginal area.
2.Remove the bottom cover and the top cap.
3.Attach the top cap to the base.
4.Press plunger gently.
5.Lie on your back with your knees bent. Gently insert the applicator into the vagina and press plunger fully to release the gel.
6.Withdraw and discard the applicator.
7.Use one applicatorful daily, preferably at bedtime.
Children under 12 years: Consult a health professional

INACTIVE INGREDIENT

WATER
LACTOBACILLUS FERMENT LYSATE

SNAKE SEED EXTRACT

ALOE VERA EXTRACT
QIAN JIN TENG EXTRACT
CARTHAMUS TINCTORIUS (SAFFLOWER) EXTRACT
LITHOSPERMUM ERYTHRORHIZON EXTRACT
COCOS NUCIFERA (COCONUT) OIL
TOCOPHERYL ACETATE
SQUALANE
SIMMONDSIA CHINENSIS (JOJOBA) SEED OIL
CARBOMER